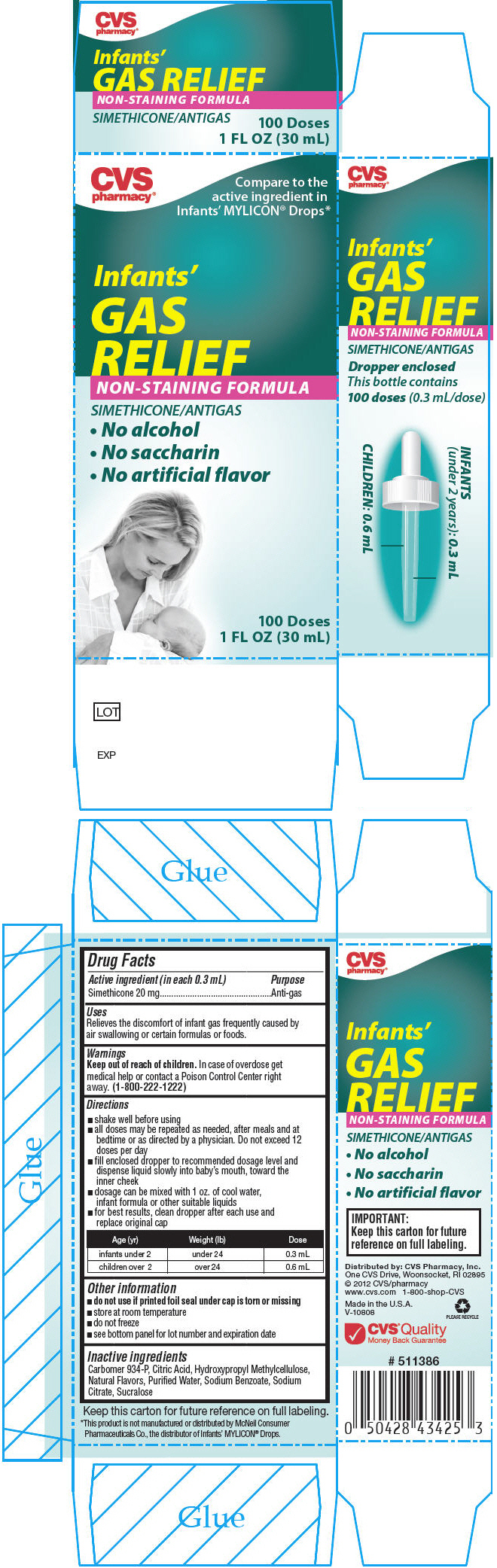 DRUG LABEL: Infants Gas Relief 
NDC: 59779-704 | Form: LIQUID
Manufacturer: CVS
Category: otc | Type: HUMAN OTC DRUG LABEL
Date: 20131204

ACTIVE INGREDIENTS: DIMETHICONE 20 mg/0.3 mL
INACTIVE INGREDIENTS: SODIUM BENZOATE; CITRIC ACID MONOHYDRATE; HYPROMELLOSES; CARBOMER HOMOPOLYMER TYPE B (ALLYL SUCROSE CROSSLINKED); SUCRALOSE; VANILLIN; SODIUM CITRATE; WATER

Infant's Gas Relief
Non-Staining Formula

Drug Facts

Active ingredient (in each 0.3 mL)

Simethicone 20 mg

Purpose

Anti-gas

Uses

Relieves the discomfort of infant gas frequently caused by air swallowing or certain formulas or foods.

Warnings

Keep out of reach of children. In case of overdose get medical help or contact a Poison Control Center right away. (1-800-222-1222)

Directions

- shake well before using
- all doses may be repeated as needed, after meals and at bedtime or as directed by a physician. Do not exceed 12 doses per day
- fill enclosed dropper to recommended dosage level and dispense liquid slowly into baby's mouth, toward the inner cheek
- dosage can be mixed with 1 oz. of cool water, infant formula or other suitable liquids
- for best results, clean dropper after each use and replace original cap

Age (yr) | Weight (lb) | Dose
infants under 2 | under 24 | 0.3 mL
children over 2 | over 24 | 0.6 mL

Other information

- do not use if printed foil seal under cap is torn or missing
- store at room temperature
- do not freeze
- see bottom panel for lot number and expiration date

Inactive ingredients

Carbomer 934-P, Citric Acid, Hydroxypropyl Methylcellulose, Natural Flavors, Purified Water, Sodium Benzoate, Sodium Citrate, Sucralose

Distributed by: CVS Pharmacy, Inc.
One CVS Drive, Woonsocket, RI 02895

PRINCIPAL DISPLAY PANEL - 30 mL Bottle Carton

CVS
pharmacy®

Compare to the
active ingredient in
Infants' MYLICON® Drops*

Infants'
GAS
RELIEF
NON-STAINING FORMULA

SIMETHICONE/ANTIGAS

- No alcohol
- No saccharin
- No artificial flavor

100 Doses
1 FL OZ (30 mL)